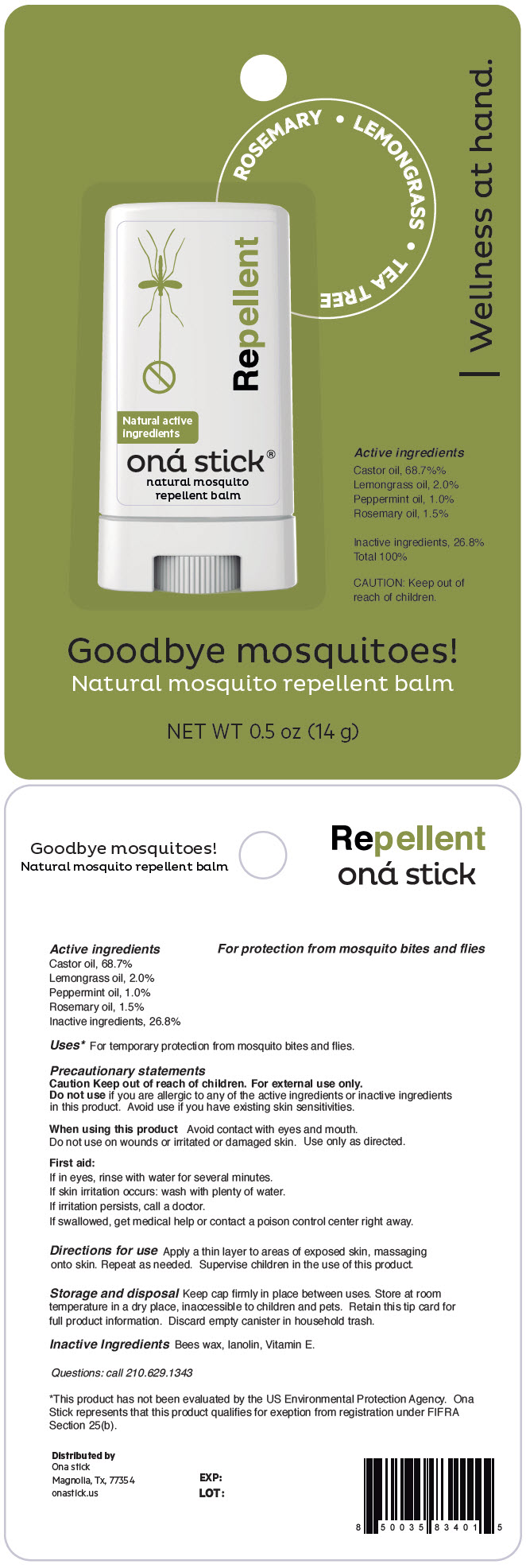 DRUG LABEL: Repellent
NDC: 82610-001 | Form: STICK
Manufacturer: ONA STICK USA LLC
Category: homeopathic | Type: HUMAN OTC DRUG LABEL
Date: 20220318

ACTIVE INGREDIENTS: castor oil 9.6 g/14 g; WEST INDIAN LEMONGRASS OIL 0.28 g/14 g; Peppermint Oil 0.14 g/14 g; Rosemary Oil 0.21 g/14 g
INACTIVE INGREDIENTS: YELLOW WAX; Lanolin; .ALPHA.-TOCOPHEROL

Repellent

Active ingredients

Castor oil, 68.7%
Lemongrass oil, 2.0%
Peppermint oil, 1.0%
Rosemary oil, 1.5%
Inactive ingredients, 26.8%

PURPOSE

For protection from mosquito bites and flies

Uses [This product has not been evaluated by the US Environmental Protection Agency. Ona Stick represents that this product qualifies for exeption from registration under FIFRA Section 25(b).]

For temporary protection from mosquito bites and flies.

Precautionary statements

KEEP OUT OF REACH OF CHILDREN

Caution Keep out of reach of children. For external use only.

Do not use if you are allergic to any of te active ingredients or inactive ingredients in this product. Avoid use if you have existing skin sensitivities.

When using this product

Avoid contact with eyes and mouth.

Do not use on wounds or irritated or damaged skin. Use only as directed.

First aid

If in eyes, rinse with water for several minutes.

If skin irritation occurs: wash with plenty of water.

If irritation persists, call a doctor.

If swallowed, get medical help or contact a poison control center right away.

Directions for use

Apply a thin layer to areas of exposed skin, massaging onto skin. Repeat as needed. Supervise children in the use of this product.

Storage and disposal

Keep cap firmly in place between uses. Store at room temperature in a dry place, inaccessible to children and pets. Retain this tip card for full product information. Discard empty canister in household trash.

Inactive Ingredients

Bees wax, lanolin, Vitamin E.

Questions

call 210.629.1343

Distributed by
Ona stick
Magnolia, Tx, 77354

PRINCIPAL DISPLAY PANEL - 14 g Tube Blister Pack

ROSEMARY • LEMONGRASS • TEA TREE

Natural active
ingredients

Repellent

oná stick®
natural mosquito
repellent balm

| Wellness at hand.

Active ingredients
Castor oil, 68.7%%
Lemongrass oil, 2.0%
Peppermint oil, 1.0%
Rosemary oil, 1.5%

Inactive ingredients, 26.8%
Total 100%

CAUTION: Keep out of
reach of children.

Goodbye mosquitoes!

Natural mosquito repellent balm

NET WT 0.5 oz (14 g)